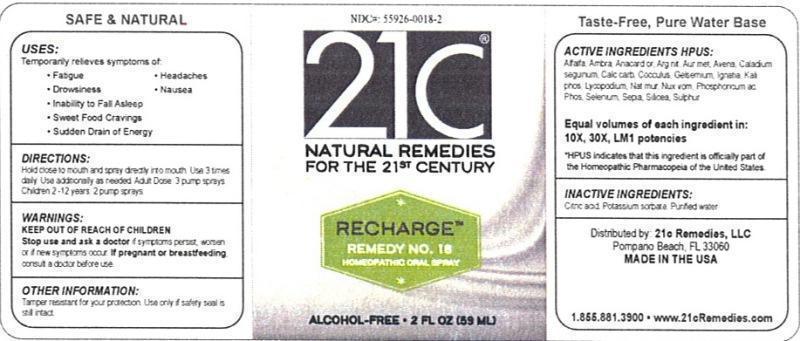 DRUG LABEL: Recharge Remedy No. 18
NDC: 55926-0018 | Form: LIQUID
Manufacturer: Speer Laboratories, LLC
Category: homeopathic | Type: HUMAN OTC DRUG LABEL
Date: 20130801

ACTIVE INGREDIENTS: ALFALFA 10 [hp_X]/59 mL; AMBERGRIS 10 [hp_X]/59 mL; SEMECARPUS ANACARDIUM JUICE 10 [hp_X]/59 mL; SILVER NITRATE 10 [hp_X]/59 mL; GOLD 10 [hp_X]/59 mL; AVENA SATIVA FLOWERING TOP 10 [hp_X]/59 mL; DIEFFENBACHIA SEGUINE 10 [hp_X]/59 mL; OYSTER SHELL CALCIUM CARBONATE, CRUDE 10 [hp_X]/59 mL; ANAMIRTA COCCULUS SEED 10 [hp_X]/59 mL; GELSEMIUM SEMPERVIRENS ROOT 10 [hp_X]/59 mL; STRYCHNOS IGNATII SEED 10 [hp_X]/59 mL; POTASSIUM PHOSPHATE, DIBASIC 10 [hp_X]/59 mL; LYCOPODIUM CLAVATUM SPORE 10 [hp_X]/59 mL; SODIUM CHLORIDE 10 [hp_X]/59 mL; STRYCHNOS NUX-VOMICA SEED 10 [hp_X]/59 mL; PHOSPHORIC ACID 10 [hp_X]/59 mL; PHOSPHORUS 10 [hp_X]/59 mL; SELENIUM 10 [hp_X]/59 mL; SEPIA OFFICINALIS JUICE 10 [hp_X]/59 mL; SILICON DIOXIDE 10 [hp_X]/59 mL; SULFUR 10 [hp_X]/59 mL
INACTIVE INGREDIENTS: CITRIC ACID MONOHYDRATE; POTASSIUM SORBATE; WATER

Recharge Remedy No. 18

ACTIVE INGREDIENT

Active Ingredients HPUS: Alfalfa, Ambra grisea, Anacardium orientale, Argentum nitricum, Aurum metallicum, Avena sativa, Caladium seguinum, Calcarea carbonica, Cocculus indicus, Gelsemium sempervirens, Ignatia amara, Kali phosphoricum, Lycopodium clavatum, Natrum muriaticum, Nux vomica, Phosphoricum acidum, Phosphorus, Selenium metallicum, Sepia, Silicea, Sulphur.

Equal volumes of each ingredient in: 10X, 30X, LM1 potencies

HPUS indicates that this ingredient is officially part of the Homeopathic Pharmacopeia of the United States.

Inactive Ingredients: Citric acid, Potassium sorbate, Purified water.

INDICATIONS AND USAGE

Uses: Temporarily relieves symptoms of:

- fatigue
- drowsiness
- inabilty to fall asleep
- sweet food cravings
- sudden drain of energy
- headaches
- nausea

Directions:

Hold close to mouth and spray directly into mouth. Use 3 times daily. Use additionally as needed. Adult dose 3 pump sprays. Children 2-12 years 2 pump sprays

Keep out of reach of children.

WARNINGS

Warnings: Stop use and ask a doctor if symptoms persist, worsen or if new symptoms occur. If pregnant or breastfeeding, consult a doctor before use.

OTHER SAFETY INFORMATION

Tamper resistant for your protection. Use only if safety seal is still intact.

PURPOSE

Uses: Temporarily relieves symptoms of: fatigue, drowsiness, inabilty to fall asleep, sweet food cravings, sudden drain of energy, headaches and nausea.